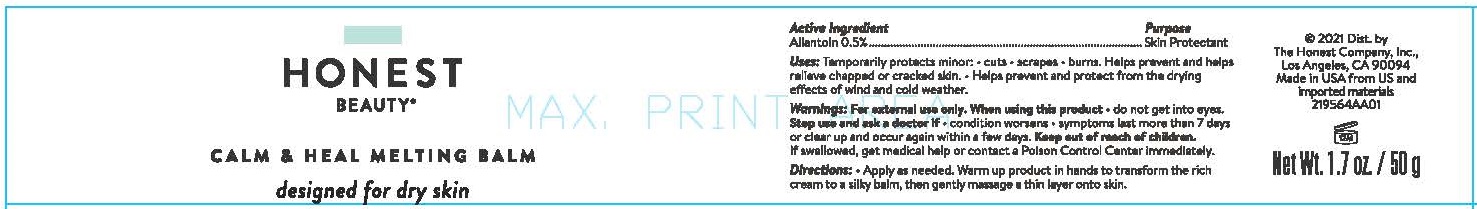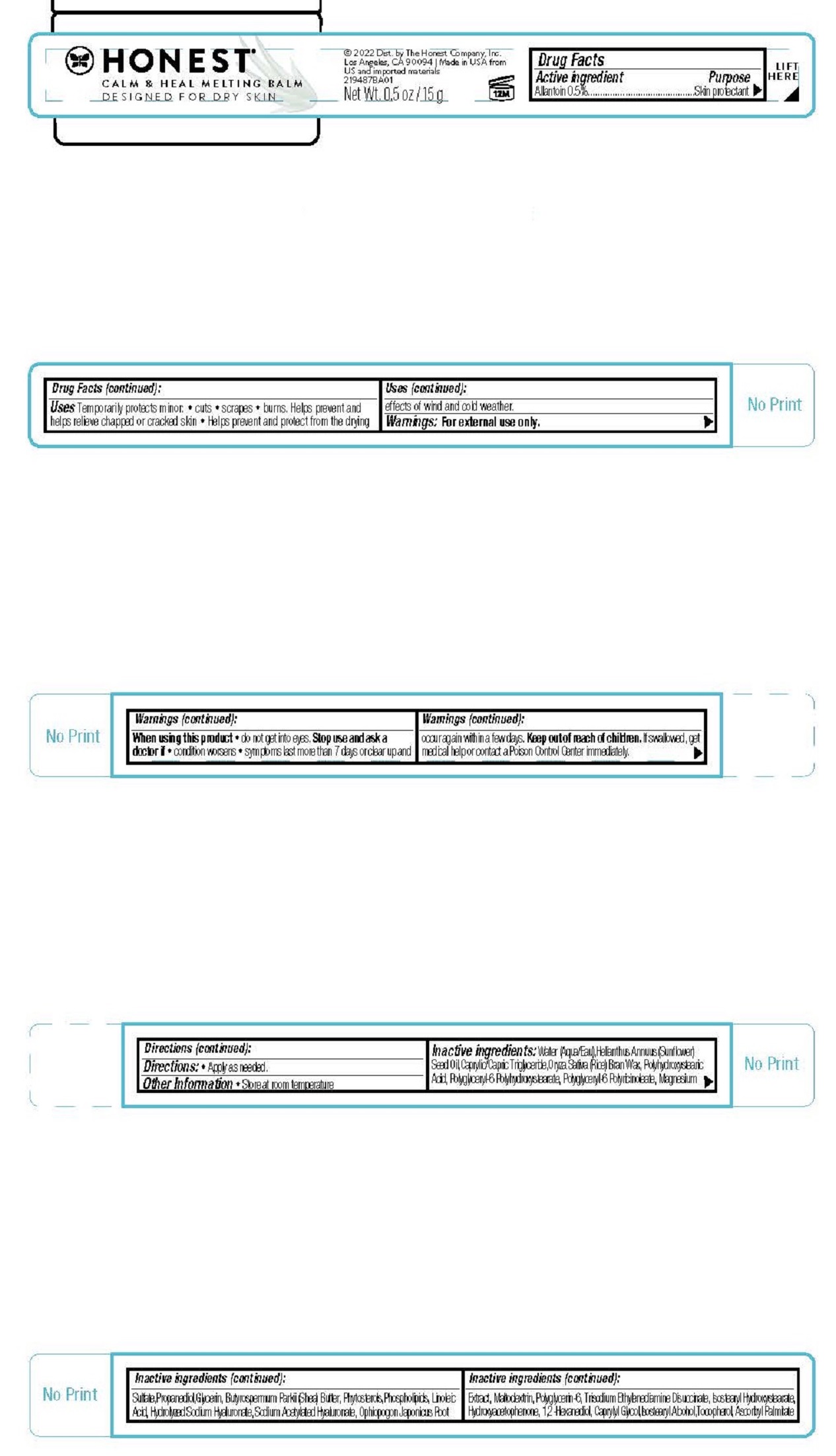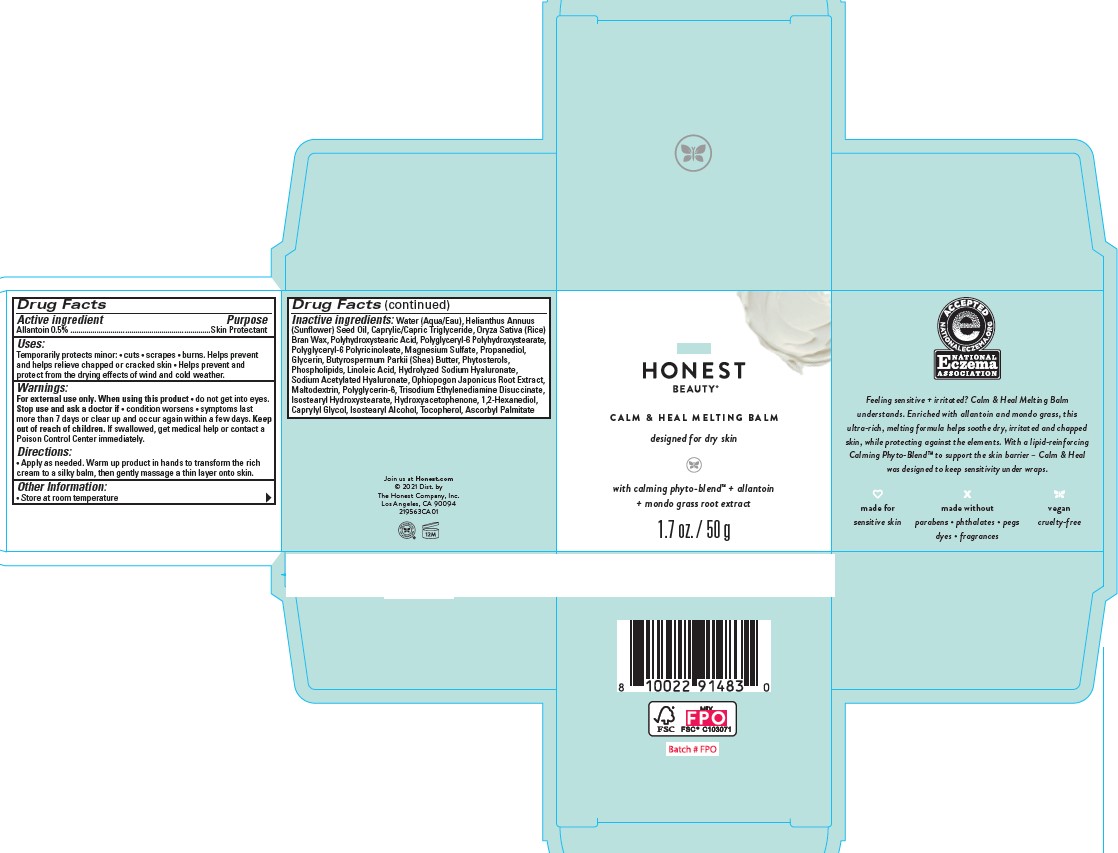 DRUG LABEL: Calm and Heal Melting Balm
NDC: 69366-505 | Form: CREAM
Manufacturer: The Honest Company, Inc.
Category: otc | Type: HUMAN OTC DRUG LABEL
Date: 20231219

ACTIVE INGREDIENTS: ALLANTOIN 0.5 g/100 g
INACTIVE INGREDIENTS: POLYHYDROXYSTEARIC ACID (2300 MW); POLYGLYCERIN-6; MEDIUM-CHAIN TRIGLYCERIDES; LECITHIN, SOYBEAN; TRISODIUM ETHYLENEDIAMINE DISUCCINATE; WATER; SUNFLOWER OIL; RICE BRAN; SOY STEROL; BUTYROSPERMUM PARKII (SHEA) BUTTER UNSAPONIFIABLES; SODIUM ACETYLATED HYALURONATE; MALTODEXTRIN; ISOSTEARYL HYDROXYSTEARATE; TOCOPHEROL; OPHIOPOGON JAPONICUS ROOT; ASCORBYL PALMITATE; MAGNESIUM SULFATE, UNSPECIFIED; HYDROXYACETOPHENONE; PROPANEDIOL; GLYCERIN; 1,2-HEXANEDIOL; CAPRYLYL GLYCOL; ISOSTEARYL ALCOHOL; POLYGLYCERYL-2 DIPOLYHYDROXYSTEARATE; LINOLEIC ACID; POLYGLYCERYL-6 POLYRICINOLEATE; HYALURONATE SODIUM

Honest Calm & Heal Melting Balm

Active ingredient Allantoin 0.5%

Purpose skin protectant

Uses

- Temporarily protects minor:

•cuts

•scrapes

•burns

- Helps prevent and helps relieve chapped or cracked skin
- Helps prevent and protect from the drying effects of wind and cold weather

Warnings For external use only

When using this product do not get into eyes.

Stop use and ask a doctor if

- condition worsens
- symptoms last more than 7 days or clear up and occur again within a few days

Keep out of reach of children If swallowed, get medical help or contact a Poison Control Center immediately

DOSAGE AND ADMINISTRATION

Directions Apply as needed. Warm up product in hands to transform the rich cream to a silky balm, then gently massage a thin layer onto skin.

Other information: Store at room temperature

INACTIVE INGREDIENT

Inactive ingredients Water (Aqua/Eau),Helianthus Annuus (Sunflower) Seed Oil,Caprylic/Capric Triglyceride,Oryza Sativa (Rice) Bran Wax,Polyhydroxystearic Acid, Polyglyceryl-6 Polyhydroxystearate, Polyglyceryl-6 Polyricinoleate, Magnesium Sulfate,Propanediol,Glycerin, Butyrospermum Parkii (Shea) Butter, Phytosterols,Phospholipids, Linoleic Acid, Hydrolyzed Sodium Hyaluronate, Sodium Acetylated Hyaluronate, Ophiopogon Japonicus Root Extract, Maltodextrin, Polyglycerin-6, Trisodium Ethylenediamine Disuccinate, Isostearyl Hydroxystearate, Hydroxyacetophenone, 1,2-Hexanediol, Caprylyl Glycol,Isostearyl Alcohol,Tocopherol, Ascorbyl Palmitate

HONEST BEAUTY®

CALM & HEAL MELTING BALM

designed for dry skin

with calming phyto-blemd™ + allantoin

+ mondo grass root extract

©2021 Dist. by

The Honest Company, Inc.

Los Angeles, CA 90094

Net Wt. 1.7 oz. / 50 g

Net Wt. 0.5 oz 15 g